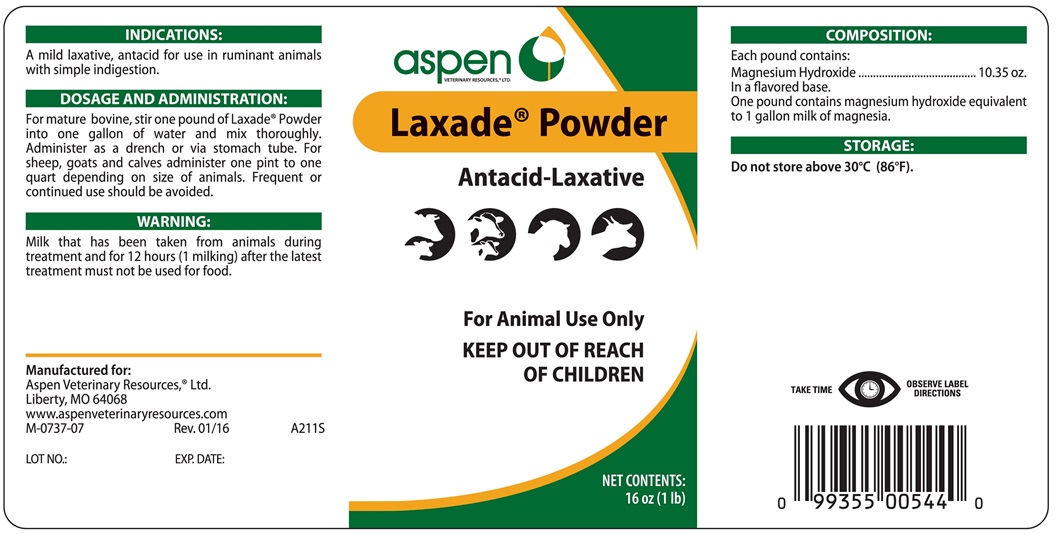 DRUG LABEL: LAXADE
NDC: 46066-280 | Form: POWDER, FOR SOLUTION
Manufacturer: Aspen Resources, Ltd.
Category: animal | Type: OTC ANIMAL DRUG LABEL
Date: 20170601

ACTIVE INGREDIENTS: MAGNESIUM HYDROXIDE 0.3 kg/0.5 kg

Laxade Powder

INDICATIONS AND USAGE

Antacid-Laxative

For Animal Use Only

KEEP OUT OF REACH OF CHILDREN

INDICATIONS

A mild laxative, antacid for use in ruminant animals with simple indigestion.

DOSAGE AND ADMINISTRATION

For mature bovine, stir one pound of laxade Powder into one gallon of water and mix thoroughly. Administer as a drench or via stomach tube. For sheep, goats and calves administer one pint to one quart depending on size of animals. Frequent or continued use should be avoided.

WARNING

Milk that has been taken from animals during treatment and for 12 hours (1 milking) after the latest treatment must not be used for food.